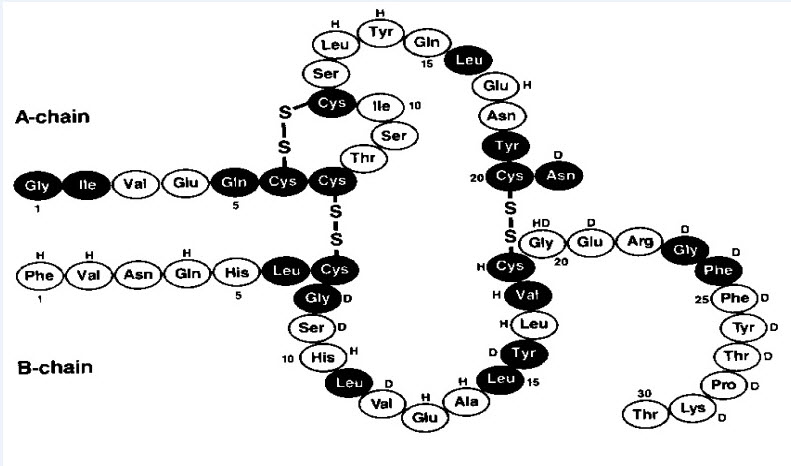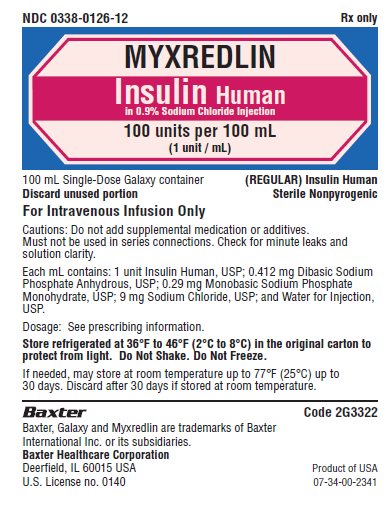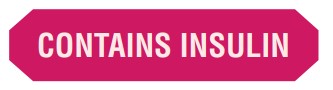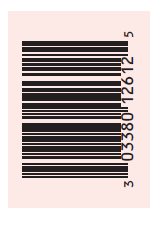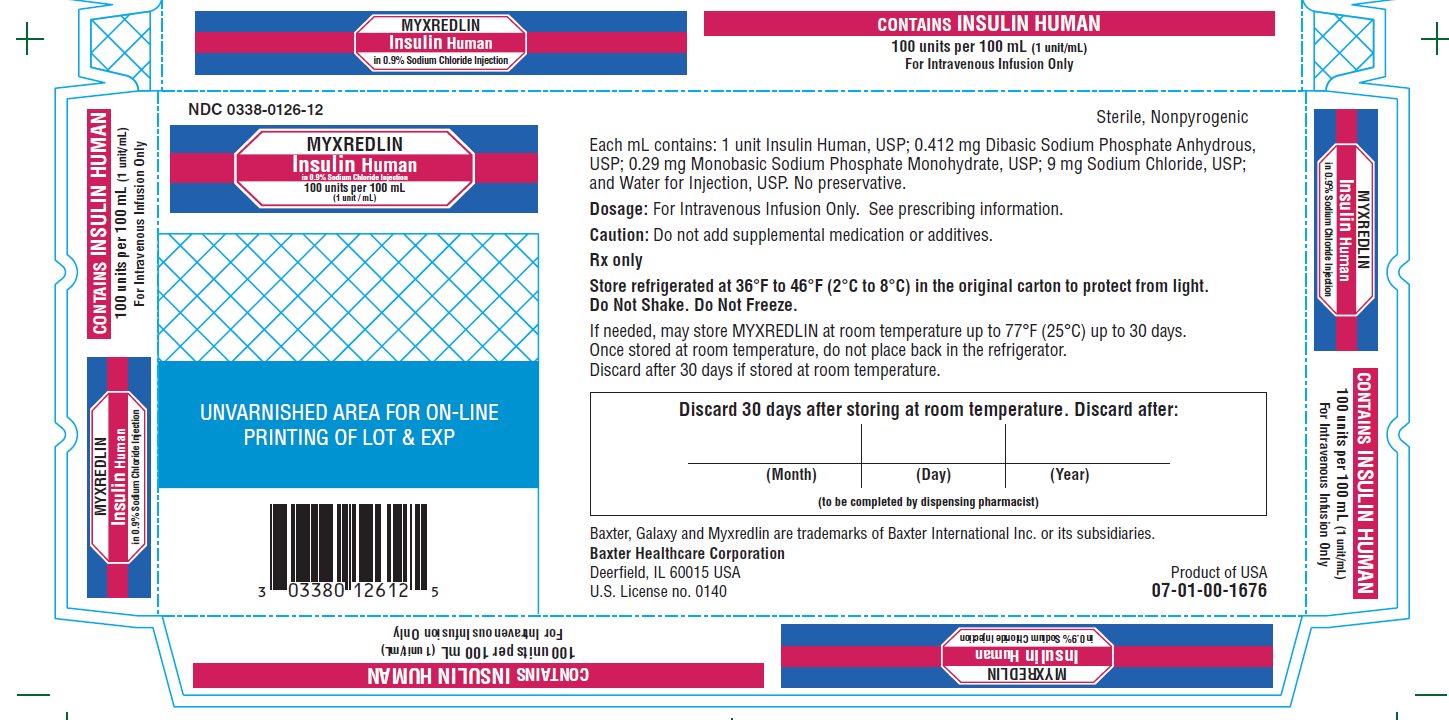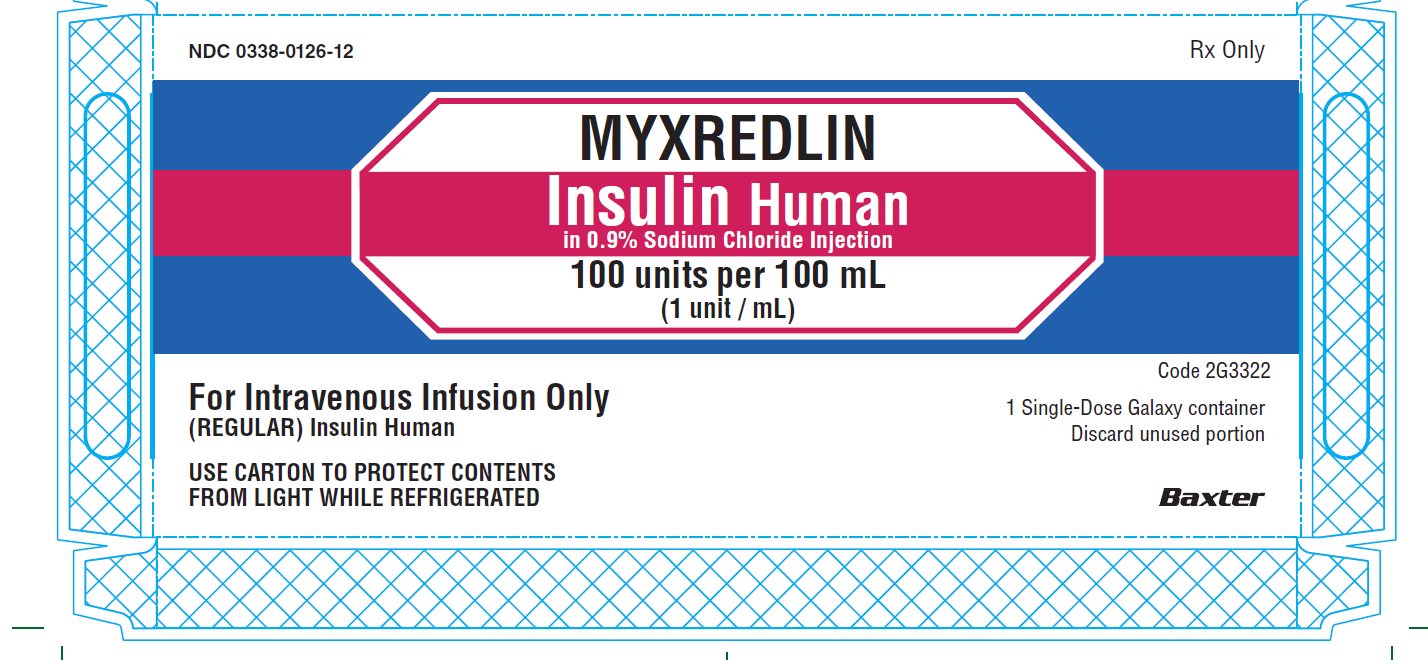 DRUG LABEL: MYXREDLIN
NDC: 0338-0126 | Form: INJECTION, SOLUTION
Manufacturer: Baxter Healthcare Corporation
Category: prescription | Type: HUMAN PRESCRIPTION DRUG LABEL
Date: 20250307

ACTIVE INGREDIENTS: INSULIN HUMAN 1.00 [iU]/1 mL
INACTIVE INGREDIENTS: SODIUM PHOSPHATE, DIBASIC, ANHYDROUS 0.412 mg/1 mL; SODIUM PHOSPHATE, MONOBASIC, MONOHYDRATE 0.29 mg/1 mL; SODIUM CHLORIDE 9 mg/1 mL; WATER

HIGHLIGHTS OF PRESCRIBING INFORMATION

These highlights do not include all the information needed to use MYXREDLIN safely and effectively. See full prescribing information for MYXREDLIN.
MYXREDLIN (insulin human) in sodium chloride injection, for intravenous use
Initial U.S. Approval: 2019

1 INDICATIONS AND USAGE

MYXREDLIN is a short-acting human insulin indicated to improve glycemic control in adults and pediatric patients with diabetes mellitus (1).

2 DOSAGE AND ADMINISTRATION

- Inspect MYXREDLIN visually before use. It should appear clear and colorless. Do not use MYXREDLIN if particulate matter or coloration is seen. (2.1)
- Administer MYXREDLIN intravenously ONLY under medical supervision with close monitoring of blood glucose and potassium levels.(2.1)
- Do not add supplementary medication or additives. (2.1)
- Do not use in series connections. (2.1)
- Do not shake or freeze. Discard unused portion. (2.1)
- Individualize dose based on metabolic needs, blood glucose monitoring results, and glycemic control goal. (2.2)
- Dosage adjustments may be needed with changes in nutrition, renal, or hepatic function or during acute illness. (2.2)

3 DOSAGE FORMS AND STRENGTHS

Injection: 100 units insulin human in 100 mL of 0.9% sodium chloride (1 unit/mL) in a single-dose container (3)

4 CONTRAINDICATIONS

- During episodes of hypoglycemia (4)
- Hypersensitivity to insulin human or any of the excipients in MYXREDLIN (4)

5 WARNINGS AND PRECAUTIONS

- Hyper- or Hypoglycemia with Changes in Insulin Regimen: Carry out under close medical supervision and increase frequency of blood glucose monitoring. (5.1)
- Hypoglycemia: May be life-threatening. Factors which may increase the risk include changes in nutrition and co-administered medication and patients with renal or hepatic impairment. Increased frequency of blood glucose monitoring is recommended in patients at increased risk. (5.2)
- Hypersensitivity Reactions: Severe, life-threatening, generalized allergy, including anaphylaxis, can occur. Discontinue MYXREDLIN, monitor, and treat if indicated. (5.3)
- Hypokalemia: May be life-threatening. Monitor potassium levels and treat if indicated. (5.4)
- Fluid Retention and Heart Failure with Concomitant Use of Thiazolidinediones (TZDs): Observe for signs and symptoms of heart failure; consider dosage reduction or discontinuation if heart failure occurs. (5.5)

6 ADVERSE REACTIONS

Adverse reactions observed with insulin human injection include hypoglycemia, allergic reactions, weight gain and edema (6).

To report SUSPECTED ADVERSE REACTIONS, contact Baxter Healthcare at 1-866-888-2472 or FDA at 1-800-FDA-1088 or www.fda.gov/medwatch.

7 DRUG INTERACTIONS

- Drugs that may increase the risk of hypoglycemia: antidiabetic agents, ACE inhibitors, angiotensin II receptor blocking agents, disopyramide, fibrates, fluoxetine, monoamine oxidase inhibitors, pentoxifylline, pramlintide, salicylates, somatostatin analog (e.g., octreotide), and sulfonamide antibiotics. (7)
- Drugs that may decrease the blood glucose lowering effect: atypical antipsychotics, corticosteroids, danazol, diuretics, estrogens, glucagon, isoniazid, niacin, oral contraceptives, phenothiazines, progestogens (e.g., in oral contraceptives), protease inhibitors, somatropin, sympathomimetic agents (e.g., albuterol, epinephrine, terbutaline), and thyroid hormones. (7)
- Drugs that may increase or decrease the blood glucose lowering effect: Alcohol, beta-blockers, clonidine, lithium salts, and pentamidine. (7)
- Drugs that may blunt the signs and symptoms of hypoglycemia: beta-blockers, clonidine, guanethidine, and reserpine. (7)

FULL PRESCRIBING INFORMATION

1 INDICATIONS AND USAGE

MYXREDLIN is indicated to improve glycemic control in adults and pediatric patients with diabetes mellitus.

2 DOSAGE AND ADMINISTRATION

2.1 Important Administration Instructions

- Inspect MYXREDLIN visually before use. It should appear clear and colorless. Do not use MYXREDLIN if particulate matter or coloration is seen.
- Administer MYXREDLIN intravenously ONLY under medical supervision with close monitoring of blood glucose and potassium levels [see Warnings and Precautions (5.2, 5.4)].
- Do not add supplementary medication or additives.
- Do not use in series connections.
- Do not shake. Do not freeze. Discard any unused portion.

2.2 Dosage Information

- Individualize and adjust the dosage of MYXREDLIN based on the individual's metabolic needs, blood glucose monitoring results, and glycemic control goal.
- Dosage adjustments may be needed with changes in nutrition, changes in renal or hepatic function or during acute illness [see Warnings and Precautions (5.1, 5.2) and Use in Specific Populations (8.6, 8.7)].

2.3 Dosage Adjustment due to Drug Interactions

- Dosage adjustment may be needed when MYXREDLIN is used concomitantly with certain drugs [see Drug Interactions (7)].

3 DOSAGE FORMS AND STRENGTHS

Injection: 100 units insulin human in 100 mL of 0.9% sodium chloride (1 unit per mL) as a clear, colorless solution in a single-dose container.

4 CONTRAINDICATIONS

MYXREDLIN is contraindicated:

- During episodes of hypoglycemia
- In patients with hypersensitivity to insulin human or any of the excipients in MYXREDLIN

5 WARNINGS AND PRECAUTIONS

5.1 Hyperglycemia or Hypoglycemia with Changes in Insulin Regimen

Changes in insulin strength, manufacturer, type, or method of administration may affect glycemic control and predispose to hypoglycemia [see Warnings and Precautions (5.2)] or hyperglycemia. These changes should be made cautiously and under close medical supervision and the frequency of blood glucose monitoring should be increased.

5.2 Hypoglycemia

Hypoglycemia is the most common adverse reaction of all insulins, including MYXREDLIN. Severe hypoglycemia can cause seizures, may lead to unconsciousness, may be life threatening or cause death. Hypoglycemia can impair concentration ability and reaction time.

Hypoglycemia can happen suddenly and symptoms may differ in each individual and change over time in the same individual. Symptomatic awareness of hypoglycemia may be less pronounced in patients with longstanding diabetes, in patients with diabetic nerve disease, in patients using medications that block the sympathetic nervous system (e.g., beta-blockers) [see Drug Interactions (7)], or in patients who experience recurrent hypoglycemia.

Risk Factors for Hypoglycemia
Factors which may increase the risk of hypoglycemia include changes in nutrition and co-administered medication [see Drug Interactions (7)]. Patients with renal or hepatic impairment may be at higher risk of hypoglycemia [see Use in Specific Populations (8.6, 8.7)].

Risk Mitigation Strategies for Hypoglycemia
Patients and caregivers must be educated to recognize hypoglycemia. In patients at higher risk for hypoglycemia and patients who have reduced symptomatic awareness of hypoglycemia, increased frequency of blood glucose monitoring is recommended.

5.3 Hypersensitivity and Allergic Reactions

Severe, life-threatening, generalized allergy, including anaphylaxis, can occur with MYXREDLIN. Generalized allergy to insulin may manifest as a whole body rash (including pruritus), dyspnea, wheezing, hypotension, tachycardia, or diaphoresis. If hypersensitivity reactions occur, discontinue MYXREDLIN; treat per standard of care and monitor until symptoms and signs resolve. MYXREDLIN is contraindicated in patients who have had hypersensitivity reactions to insulin human or any of the excipients in MYXREDLIN [see Contraindications (4)].

5.4 Hypokalemia

All insulins, including MYXREDLIN, cause a shift in potassium from the extracellular to intracellular space, possibly leading to hypokalemia. Untreated hypokalemia may cause respiratory paralysis, ventricular arrhythmia, and death. Monitor potassium levels and treat if indicated.

5.5 Fluid Retention and Heart Failure with Concomitant Use of PPAR-gamma agonists

Thiazolidinediones (TZDs), which are peroxisome proliferator-activated receptor (PPAR)-gamma agonists, can cause dose-related fluid retention, particularly when used in combination with insulin. Fluid retention may lead to or exacerbate heart failure. Patients treated with insulin, including MYXREDLIN, and a PPAR-gamma agonist should be observed for signs and symptoms of heart failure. If heart failure develops, it should be managed according to current standards of care, and discontinuation or dose reduction of the PPAR-gamma agonist must be considered.

6 ADVERSE REACTIONS

The following adverse reactions are also discussed elsewhere in the labeling:

- Hypoglycemia [see Warnings and Precautions (5.2)]
- Hypersensitivity Reactions [see Warnings and Precautions (5.3)]
- Hypokalemia [see Warnings and Precautions (5.4)]

Adverse Reactions from Clinical Studies or Postmarketing Reports
The following additional adverse reactions have been identified during clinical studies or from postmarketing reports with use of insulin human injection. Because some of these reactions are reported voluntarily from a population of uncertain size, it is not always possible to reliably estimate their frequency or to establish a causal relationship to drug exposure.

Adverse reactions associated with insulin initiation and glucose control intensification
Intensification or rapid improvement in glucose control has been associated with a transitory, reversible ophthalmologic refraction disorder, worsening of diabetic retinopathy, and acute painful peripheral neuropathy. Over the long-term, improved glycemic control decreases the risk of diabetic retinopathy and neuropathy.

Hypersensitivity reactions
Severe, life-threatening, generalized allergy, including anaphylaxis.

Hypoglycemia
Hypoglycemia is the most commonly observed adverse reaction with MYXREDLIN.

Hypokalemia
MYXREDLIN can cause a shift in potassium from the extracellular to intracellular space, possibly leading to hypokalemia.

Peripheral edema
Insulins, including MYXREDLIN, may cause sodium retention and edema, particularly if previously poor metabolic control is improved by intensified insulin therapy.

Weight gain
Weight gain can occur with insulin therapies, including MYXREDLIN, and has been attributed to the anabolic effects of insulin and the decrease in glucosuria.

Immunogenicity
As with all therapeutic peptides, insulin administration may cause anti-insulin antibodies to form. Increases in titers of anti-insulin antibodies that react with human insulin have been observed in patients treated with subcutaneous insulin human injection.

7 DRUG INTERACTIONS

Table 1: Clinically Significant Drug Interactions with MYXREDLIN
Drugs that May Increase the Risk of Hypoglycemia
Drugs: | Antidiabetic agents, ACE inhibitors, angiotensin II receptor blocking agents, disopyramide, fibrates, fluoxetine, monoamine oxidase inhibitors, pentoxifylline, pramlintide, salicylates, somatostatin analog (e.g., octreotide), and sulfonamide antibiotics.
Intervention: | Dose adjustment and increased frequency of glucose monitoring may be required when MYXREDLIN is co-administered with these drugs.
Drugs that May Decrease the Blood Glucose Lowering Effect of MYXREDLIN
Drugs: | Atypical antipsychotics (e.g., olanzapine and clozapine), corticosteroids, danazol, diuretics, estrogens, glucagon, isoniazid, niacin, oral contraceptives, phenothiazines, progestogens (e.g., in oral contraceptives), protease inhibitors, somatropin, sympathomimetic agents (e.g., albuterol, epinephrine, terbutaline), and thyroid hormones.
Intervention: | Dose adjustment and increased frequency of glucose monitoring may be required when MYXREDLIN is co-administered with these drugs.
Drugs that May Increase or Decrease the Blood Glucose Lowering Effect of MYXREDLIN
Drugs: | Alcohol, beta-blockers, clonidine, and lithium salts. Pentamidine may cause hypoglycemia, which may sometimes be followed by hyperglycemia.
Intervention: | Dose adjustment and increased frequency of glucose monitoring may be required when MYXREDLIN is co-administered with these drugs.
Drugs that May Blunt Signs and Symptoms of Hypoglycemia
Drugs: | Beta-blockers, clonidine, guanethidine, and reserpine.
Intervention: | Increased frequency of glucose monitoring may be required when MYXREDLIN is co-administered with these drugs.

8 USE IN SPECIFIC POPULATIONS

8.1 Pregnancy

Risk Summary
Available data from published studies over decades have not established an association with human insulin use during pregnancy and major birth defects, miscarriage or adverse maternal or fetal outcomes (see Data). There are risks to the mother and fetus associated with poorly controlled diabetes in pregnancy (see Clinical Considerations). Animal reproduction studies were not performed.

The estimated background risk of major birth defects is 6-10% in women with pre-gestational diabetes with a HbA1c >7 and has been reported to be as high as 20-25% in women with a HbA1c >10. The estimated background risk of miscarriage for the indicated population is unknown. In the U.S. general population, the estimated background risk of major birth defects and miscarriage in clinically recognized pregnancies is 2-4% and 15-20%, respectively.

Clinical Considerations
Disease-associated maternal and/or embryo/fetal risk

Poorly controlled diabetes in pregnancy increases the maternal risk for diabetic ketoacidosis, preeclampsia, spontaneous abortions, preterm delivery, and delivery complications. Poorly controlled diabetes increases the fetal risk for major birth defects, stillbirth, and macrosomia-related morbidity.

Data
Human Data

While available studies cannot definitively establish the absence of risk, published data from retrospective studies, open-label, randomized, parallel studies and meta-analyses have not established an association with human insulin use during pregnancy and major birth defects, miscarriage, or adverse maternal or fetal outcomes. All available studies have methodological limitations including lack of blinding, unclear methods of randomization, and small sample size.

8.2 Lactation

Risk Summary
Available data from published literature suggest that exogenous human insulin products, including insulin human injection, are transferred into human milk. There are no adverse reactions reported in the breastfed infants in the literature. There are no data on the effects of exogenous human insulin products, including MYXREDLIN, on milk production. The developmental and health benefits of breastfeeding should be considered along with the mother’s clinical need for MYXREDLIN and any potential adverse effects on the breastfed infant from MYXREDLIN or from the underlying maternal condition.

8.4 Pediatric Use

MYXREDLIN is indicated to improve glycemic control in pediatric patients with diabetes mellitus.

The dosage of MYXREDLIN must be individualized in pediatric patients based on metabolic needs and frequent monitoring of blood glucose to reduce the risk of hypoglycemia [see Dosage and Administration (2.2) and Warnings and Precautions (5.2)].

8.5 Geriatric Use

The effect of age on the pharmacokinetics and pharmacodynamics of insulin human injection has not been studied.

Elderly patients using MYXREDLIN, may be at increased risk of hypoglycemia due to co-morbid disease [see Warnings and Precautions (5.2)].

8.6 Renal Impairment

The effect of renal impairment on the pharmacokinetics and pharmacodynamics of MYXREDLIN has not been studied. Patients with renal impairment are at increased risk of hypoglycemia and may require more frequent MYXREDLIN dose adjustment and more frequent blood glucose monitoring [see Warnings and Precautions (5.2)].

8.7 Hepatic Impairment

The effect of hepatic impairment on the pharmacokinetics and pharmacodynamics of MYXREDLIN has not been studied. Patients with hepatic impairment are at increased risk of hypoglycemia and may require more frequent MYXREDLIN dose adjustment and more frequent blood glucose monitoring [see Warnings and Precautions (5.2)].

10 OVERDOSAGE

Excess insulin administration may cause hypoglycemia and hypokalemia. More severe episodes with coma, seizure, or neurologic impairment can be treated with intramuscular or subcutaneous glucagon or intravenous glucose. Sustained monitoring may be necessary because hypoglycemia may recur after apparent clinical recovery. Hypokalemia must be corrected appropriately. [see Warnings and Precautions (5.2, 5.4)]

11 DESCRIPTION

Insulin human is a short-acting human insulin. It is a polypeptide hormone and is produced by recombinant DNA technology, utilizing Pichia pastoris (a yeast) as the production organism. Insulin human is regular human insulin and has the empirical formula C257H383N65O77S6 and a molecular weight of 5808.

Figure 1: Structural formula of Insulin Human

MYXREDLIN (insulin human) in 0.9% sodium chloride injection for intravenous use is a sterile, preservative-free, nonpyrogenic, clear, aqueous, and colorless solution supplied in a 100 mL GALAXY single-dose container. MYXREDLIN contains 100 units of insulin human in 100 milliliters of 0.9% sodium chloride injection. Each milliliter of solution contains 1 unit Insulin Human, USP; 0.412 mg Dibasic Sodium Phosphate Anhydrous, USP; 0.29 mg Monobasic Sodium Phosphate Monohydrate, USP; 9 mg Sodium Chloride, USP; and Water for Injection, USP. The pH range is 6.5-7.2.

12 CLINICAL PHARMACOLOGY

12.1 Mechanism of Action

The primary activity of insulin, including MYXREDLIN is the regulation of glucose metabolism. Insulins lower blood glucose by stimulating peripheral glucose uptake, especially by skeletal muscle and fat, and by inhibiting hepatic glucose production. Insulin inhibits lipolysis and proteolysis, and enhances protein synthesis.

12.2 Pharmacodynamics

MYXREDLIN is a short-acting insulin. The time course of insulin action (i.e., glucose lowering) may vary considerably in different individuals, within the same individual, and different doses. In a double-blind, randomized, crossover, euglycemic glucose clamp study described below, the average onset of action, defined as start of intravenous glucose infusion during the clamp, was approximately 21 minutes after starting of the intravenous infusion administration. The glucose infusion rate gradually increased to a maximum response of 13.7 mg/kg/min after 5 hours of human insulin infusion.

12.3 Pharmacokinetics

In a double-blind, randomized, crossover, euglycemic glucose clamp study, fifty eight healthy male subjects between 19 and 50 years of age received an intravenous infusion of either MYXREDLIN or another human insulin at 1 milliUnit/kg/min for 6 hours (0.36 units/kg total dose). On average, insulin concentrations of about 300 pM were attained approximately from 1.5 hours to 6 hours after starting intravenous infusion of MYXREDLIN, followed by a return to the baseline level 1.5 hours after stopping intravenous infusion.

Metabolism and Elimination

The mean terminal half-life from concentration data after stopping the intravenous infusion was estimated to be 23.4 minutes in healthy volunteers.

Specific Population

The effects of gender, age, obesity, renal and hepatic impairment on the pharmacodynamics and pharmacokinetics of insulin human injection have not been studied.

13 NONCLINICAL TOXICOLOGY

13.1 Carcinogenesis, Mutagenesis, Impairment of Fertility

Standard 2-year carcinogenicity studies in animals have not been performed to evaluate the carcinogenic potential of insulin human injection.

Human insulin is not mutagenic in the following in vitro tests: The chromosomal aberration assay in human lymphocytes, the micronucleus assay in mouse polychromatic erythrocytes, and the mutation frequency assay in Chinese hamster cells.

Standard reproduction and teratology studies in animals, including fertility assessments have not been conducted with insulin human injection.

16 HOW SUPPLIED/STORAGE AND HANDLING

16.1 How Supplied

MYXREDLIN (insulin human) in 0.9% sodium chloride injection contains 100 units/100 mL (1 unit/mL) of insulin human in 0.9% sodium chloride and is a clear, colorless solution available as:

100 mL single-dose GALAXY container, package of 12, NDC 0338-0126-12

16.2 Storage and Handling

Store MYXREDLIN in the refrigerator (36°F to 46°F [2°C to 8°C]) in the original carton to protect from light. Do not use after the expiration date printed on the carton and container label.

If needed, MYXREDLIN may be removed from the original carton and stored at room temperature up to 77°F (25°C) for up to 30 days. Once stored at room temperature, do not place back in the refrigerator. Discard MYXREDLIN after 30 days if stored at room temperature.

Do not freeze and do not use MYXREDLIN if it has been frozen. Do not shake.

17 PATIENT COUNSELING INFORMATION

Hypoglycemia

Inform patients that hypoglycemia is the most common adverse reaction with insulin. Inform patients that their ability to concentrate and react may be impaired as a result of hypoglycemia.

Hypersensitivity Reactions

Advise patients that hypersensitivity reactions have occurred with insulin human injection [see Warnings and Precautions (5.3)].

Manufactured by:
Baxter Healthcare Corporation
Deerfield, IL 60015 USA

U.S. License Number 0140

Baxter, Galaxy and Myxredlin are registered trademarks of Baxter International Inc.

07-19-01-720

PACKAGE/LABEL PRINCIPAL DISPLAY PANEL

Container Label

NDC 0338-0126-12 Rx only

MYXREDLIN
Insulin Human
in 0.9% Sodium Chloride Injection
100 units per 100 mL
(1 unit / mL)

100 mL Single-Dose Galaxy container (REGULAR) Insulin Human
Discard unused portion Sterile Nonpyrogenic

For Intravenous Infusion Only

Cautions: Do not add supplemental medication or additives.
Must not be used in series connections. Check for minute leaks and
solution clarity.

Each mL contains: 1 unit Insulin Human, USP; 0.412 mg Dibasic Sodium
Phosphate Anhydrous, USP; 0.29 mg Monobasic Sodium Phosphate
Monohydrate, USP; 9 mg Sodium Chloride, USP; and Water for Injection,
USP.

Dosage: See prescribing information.

Store refrigerated at 36°F to 46°F (2°C to 8°C) in the original carton to
protect from light. Do Not Shake. Do Not Freeze.

If needed, may store at room temperature up to 77°F (25°C) up to
30 days. Discard after 30 days if stored at room temperature.

Baxter logo Code 2G3322

Baxter, Galaxy and Myxredlin are trademarks of Baxter
International Inc. or its subsidiaries
Baxter Healthcare Corporation
Deerfield, IL 60015 USA
U.S. License no. 0140

Product of USA
07-34-00-2341

CONTAINS INSULIN

303380126125

Carton Label

MYXREDLIN
Insulin Human
in 0.9% Sodium Chloride Injection

CONTAINS INSULIN HUMAN
100 units per 100 mL (1 unit/mL)
For Intravenous Infusion Only

MYXREDLIN
Insulin Human
in 0.9% Sodium Chloride Injection

CONTAINS INSULIN HUMAN
100 units per 100 mL (1 unit/mL)
For Intravenous Infusion Only

NDC 0338-0126-12

MYXREDLIN
Insulin Human
in 0.9% Sodium Chloride Injection
100 units per 100 mL
(1 unit / mL)

UNVARNISHED AREA FOR ON-LINE
PRINTING OF LOT AND EXP

303380126125

Sterile, Nonpyrogenic

Each mL contains: 1 unit Insulin Human, USP; 0.412 mg Dibasic Sodium Phosphate Anhydrous,
USP; 0.29 mg Monobasic Sodium Phosphate Monohydrate, USP; 9 mg Sodium Chloride, USP;
and Water for Injection, USP. No preservative.

Dosage: For Intravenous Infusion Only. See prescribing information.

Caution: Do not add supplemental medication or additives.

Rx only

Store refrigerated at 36°F to 46°F (2°C to 8°C) in the original carton to protect from light.
Do Not Shake. Do Not Freeze.

If needed, may store MYXREDLIN at room temperature up to 77°F (25°C) up to 30 days.
Once stored at room temperature, do not place back in the refrigerator.
Discard after 30 days if stored at room temperature.

Discard 30 days after storing at room temperature. Discard After:

(Month) (Day) (Year)

(to be completed by dispensing pharmacist)

Baxter, Galaxy and Myxredlin are trademarks of Baxter International Inc. or its subsidiaries.

Baxter Healthcare Corporation

Deerfield, IL 60015 USA

U.S. License no. 0140

Product of USA
07-01-00-1676

MYXREDLIN

Insulin Human
in 0.9% Sodium Chloride Injection

CONTAINS INSULIN HUMAN
100 units per 100 mL (1 unit/mL)
For Intravenous Infusion Only

MYXREDLIN

Insulin Human
in 0.9% Sodium Chloride Injection

CONTAINS INSULIN HUMAN
100 units per 100 mL (1 unit/mL)
For Intravenous Infusion Only

NDC 0338-0126-12 Rx Only

MYXREDLIN
Insulin Human
in 0.9% Sodium Chloride Injection
100 units per 100 mL
(1 unit/mL)

For Intravenous Infusion Only
(REGULAR) Insulin Human

USE CARTON TO PROTECT CONTENTS
FROM LIGHT WHILE REFRIGERATED

Code 2G3322

1 Single-Dose GALAXY container
Discard unused portion

Baxter Logo

G